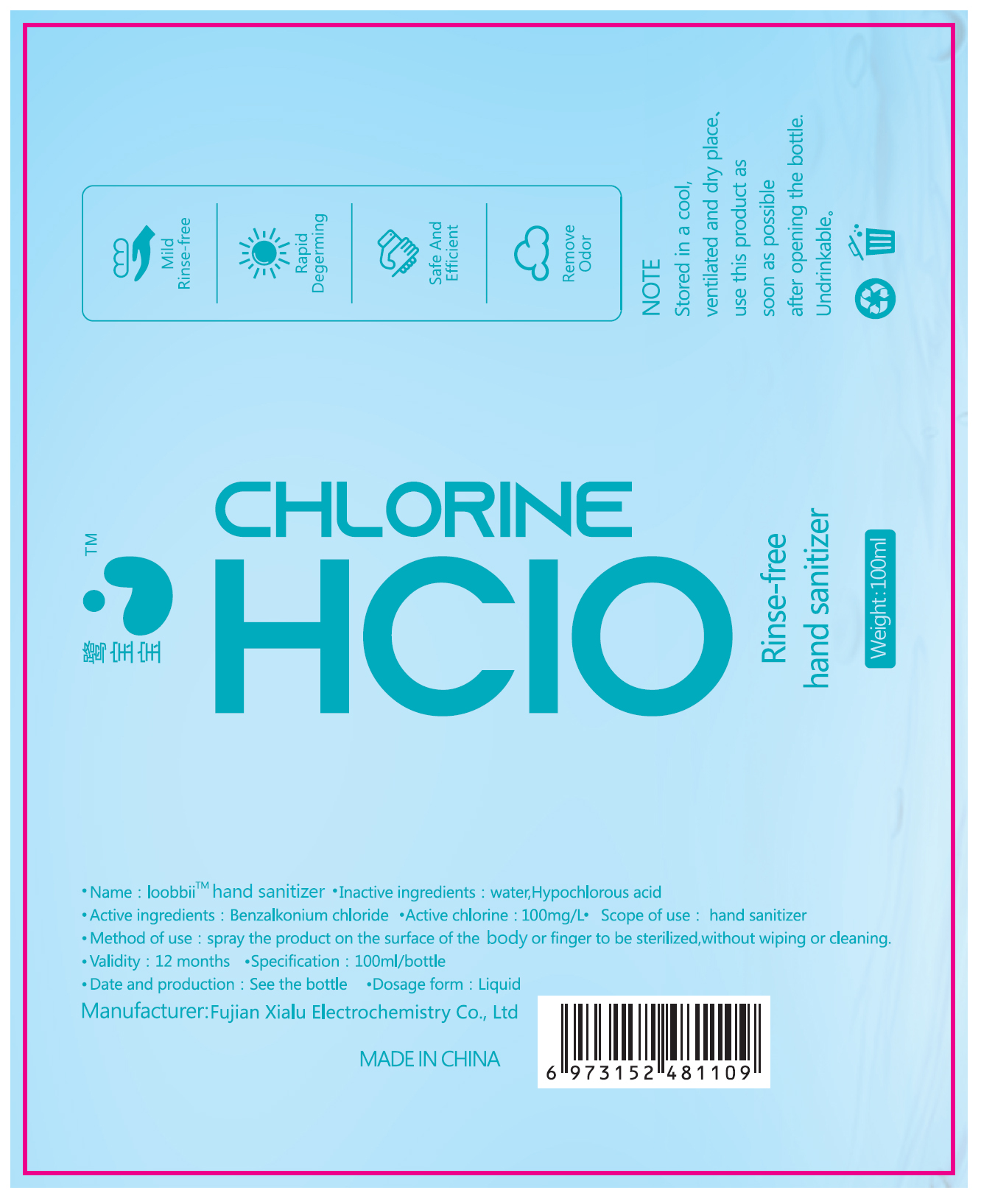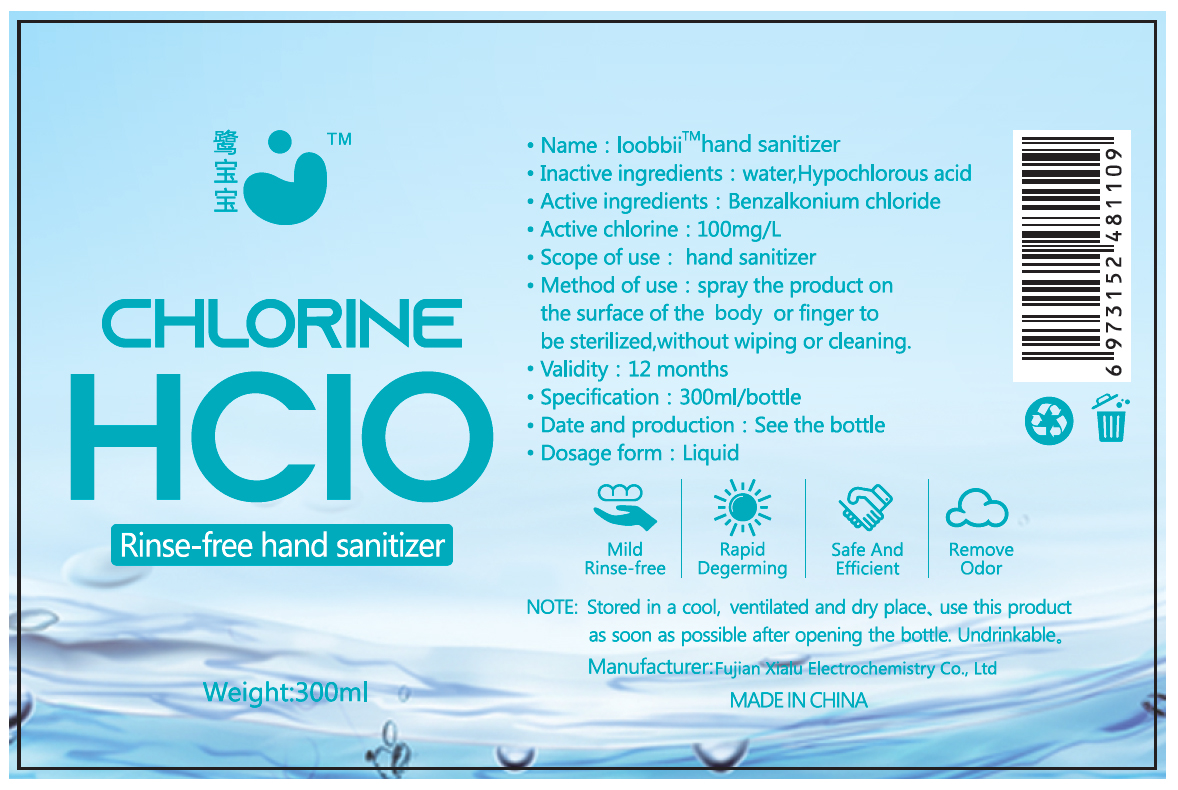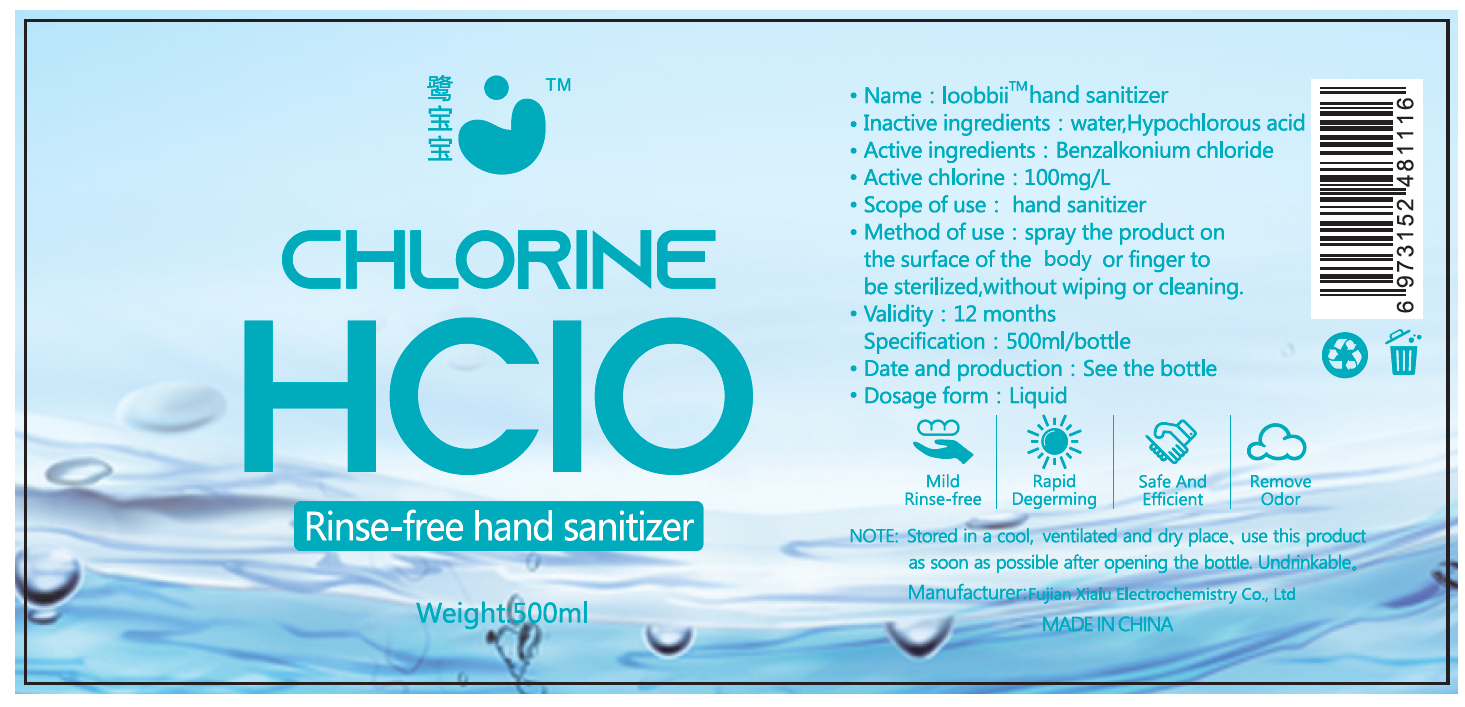 DRUG LABEL: Hand sanitizer
NDC: 75434-001 | Form: LIQUID
Manufacturer: Fujian Xialu Electrochemical Co., Ltd.
Category: otc | Type: HUMAN OTC DRUG LABEL
Date: 20200829

ACTIVE INGREDIENTS: BENZALKONIUM CHLORIDE 0.01 g/100 mL
INACTIVE INGREDIENTS: WATER; HYPOCHLOROUS ACID

Spray Hand sanitizer

Active Ingredients

Benzalkonium chloride

Purpose

Antiseptic

Use

Hand sanitizer

Warnings

STORED IN A COOL,VENTILATED AND DRY PLACE ,USE THIS PRODUCT AS SOON AS POSSIBLE AFTER OPENING THE BOTTLE.UNDRINKABLE.

DO NOT USE

Undrinkable

KEEP OUT OF REACH OF CHILDREN

Undrinkable

Directions

Spray the product evenly on the surface of the object or finger to be sterilized,without wiping or cleaning.

Other information

STORED IN A COOL,VENTILATED AND DRY PLACE ,USE THIS PRODUCT AS SOON AS POSSIBLE AFTER OPENING THE BOTTLE.

Validity: 12 months

Date and production: See the bottle.

Dosage form: Liquid

Inactive ingredients

water, hypochlorous acid

Package Label - Principal Display Panel

100ml 75434-001-01

CHLORINE

HCLO

Rinse-free

hand sanitizer

weight: 100ml

Mild Rinse-free

Rapid Degerming

Safe And Efficient

Remove Odor

300ml 75434-001-02

CHLORINE

HCLO

Rinse-free

hand sanitizer

weight: 300ml

Mild Rinse-free

Rapid Degerming

Safe And Efficient

Remove Odor

500ml 75434-001-03

CHLORINE

HCLO

Rinse-free

hand sanitizer

weight: 500ml

Mild Rinse-free

Rapid Degerming

Safe And Efficient

Remove Odor